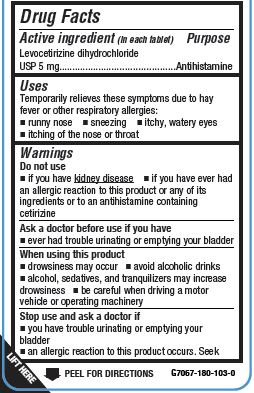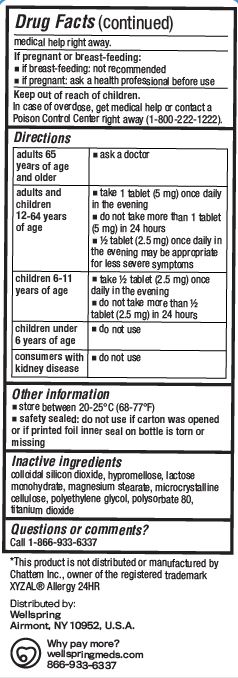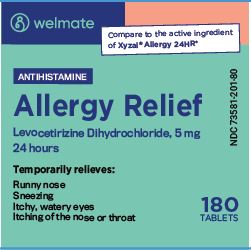 DRUG LABEL: ALLERGY RELIEF
NDC: 73581-201 | Form: TABLET
Manufacturer: YYBA CORP
Category: otc | Type: HUMAN OTC DRUG LABEL
Date: 20251203

ACTIVE INGREDIENTS: LEVOCETIRIZINE DIHYDROCHLORIDE 5 mg/1 1
INACTIVE INGREDIENTS: SILICON DIOXIDE; HYPROMELLOSE, UNSPECIFIED; LACTOSE MONOHYDRATE; MAGNESIUM STEARATE; MICROCRYSTALLINE CELLULOSE; POLYETHYLENE GLYCOL, UNSPECIFIED; POLYSORBATE 80; TITANIUM DIOXIDE

YYBA - WELMATE ALLERGY RELIEF - LEVOCETRIZINE DIHYDROCHLORIDE, 5 MG (73581-201)

Active ingredient (in each tablet)

LEVOCETIRIZINE DIHYDROCHLORIDE USP 5 MG

Purpose

Antihistamine

Uses

Temporarily relieves these symptoms due to hay fever or other upper respiratory allergies:

- runny nose
- sneezing
- itchy, watery eyes
- itching of the nose or throat

Warnings

Do not use

- if you have kidney disease
- if you have ever had an allergic reaction to this product or any of its ingredients or to an antihistamine containing cetirizine

Ask a doctor before use if you have

- ever had trouble urinating or emptying your bladder

When using this product

- drowsiness may occur
- avoid alcoholic drinks
- alcohol, sedatives, and tranquilizers may increase drowsiness
- be careful when driving a motor vehicle or operating machinery

Stop use and ask a doctor if

- you have trouble urinating or emptying your bladder
- an allergic reaction to this product occurs. Seek medical help right away.

If pregnant or breast-feeding:

- if breast-feeding: not recommended
- if pregnant: ask a health professional before use

Keep out of reach of children.
In case of overdose, get medical help or contact a Poison Control Center right away (1-800-222-1222).

Directions

ADULTS 65 YEARS OF AGE AND OLDER

- ASK A DOCTOR

ADULTS AND CHILDREN 12-64 YEARS OF AGE

- take 1 tablet (5 mg) once daily in the evening
- do not take more than 1 tablet (5 mg) in 24 hours
- ½ tablet (2.5 mg) once daily in the evening may be appropriate for less severe symptoms

CHILDREN 6-11 YEARS OF AGE

- take ½ tablet (2.5 mg) once daily in the evening
- do not take more than ½ tablet (2.5 mg) in 24 hours

CHILDREN UNDER 6 YEARS OF AGE

- DO NOT USE

CONSUMERS WITH KIDNEY DISEASE

- DO NOT USE

Other information

- store between 20-25°C (68-77°F)
- safety sealed: do not use if carton was opened or if printed foil inner seal on bottle is torn or missing

Inactive ingredients

colloidal silicon dioxide, hypromellose, lactose monohydrate, magnesium stearate, microcrystalline cellulose, polyethylene glycol, polysorbate 80, titanium dioxide

Questions?

CALL 1-866-933-6337